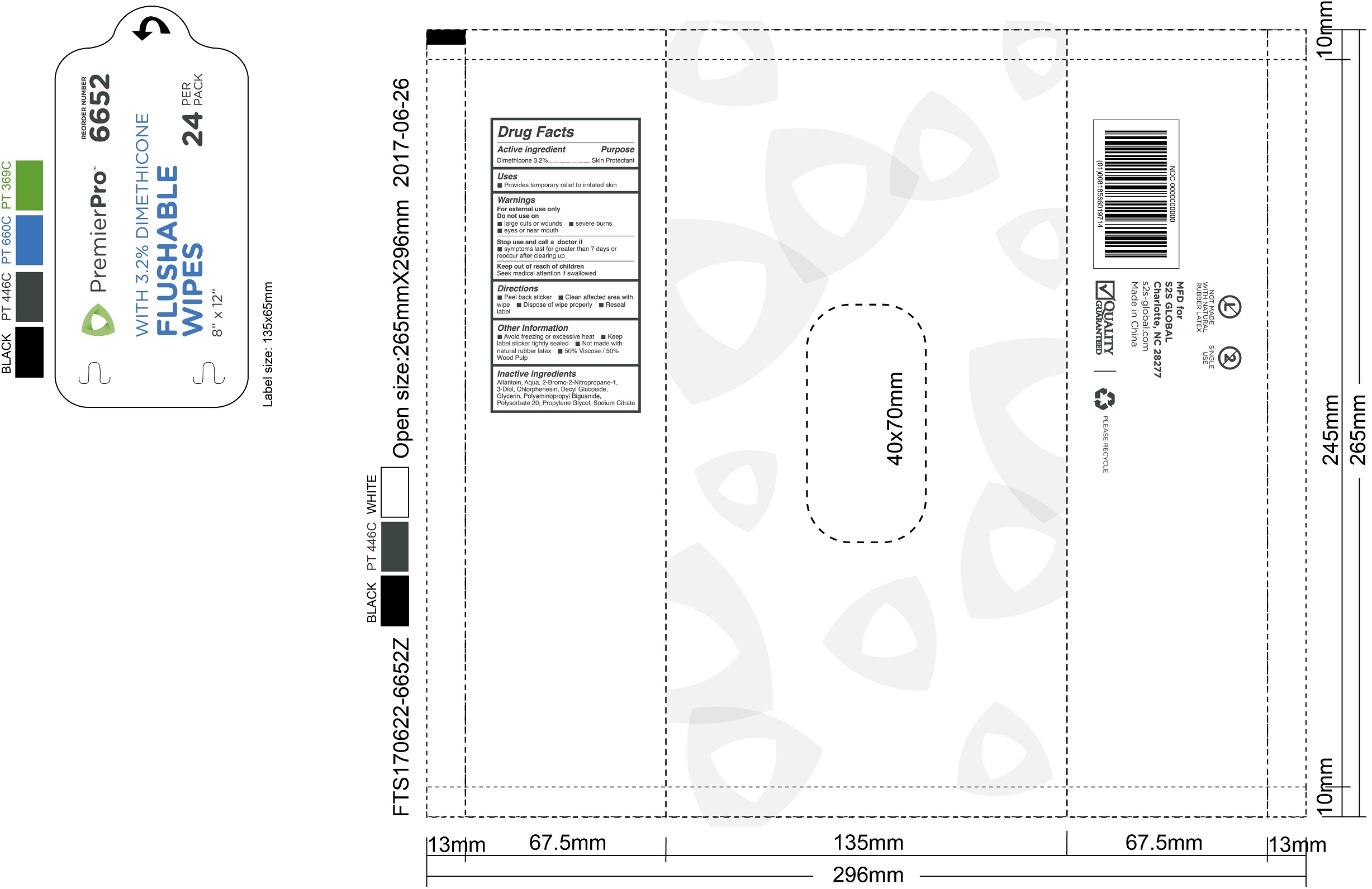 DRUG LABEL: PremierPro Flushable Wipes with Dimethicone
NDC: 61312-010 | Form: SWAB
Manufacturer: HANGZHOU GUOGUANG TOURING COMMODITY CO., LTD.
Category: otc | Type: HUMAN OTC DRUG LABEL
Date: 20180109

ACTIVE INGREDIENTS: DIMETHICONE 32 mg/1 g
INACTIVE INGREDIENTS: WATER; GLYCERIN; PROPYLENE GLYCOL; POLYSORBATE 20; ALLANTOIN; CHLORPHENESIN; DECYL GLUCOSIDE; SODIUM CITRATE

61312-010 PremierPro Flushable Wipes with Dimethicone
Personal Cleansing Cloths with Dimethicone, 42 count

Active Ingredient

Dimethicone 3.2%

Purpose

Skin Protectant

Uses:

Helps treat and prevent diaper rash. Protects chafed skin associated with diaper rash and helps protect from wetness. Temporarily protects and helps relieve chapped or cracked skin.

Warnings:

For external use only.

- Avoid contact with the eyes

Stop use

and contact a physician if condition worsens, symptoms last more than 7 days or clear up and occur again within a few days.

Keep out of reach of children

If swallowed, get medical help or contact Poison Control Center right away.

Do not use:

• On deep or puncture wounds • Animal bites • Serious burns

Directions:

Pull back label and remove wipes

• Thoroughly cleanse soiled area, using one wipe at a time

•Use as often as necessary

•Dispose of cloths in a waste receptacle

•Do not flush

Heating Instructions:

• Wipes may be used at room temperature but if heating is desired, wipes may be warmed in a wipes warmer. Wipes should be warmed:

• in a single warming session at temperatures not exceeding 52°C (125°F) and

• for a maximum of 4 days. Discard wipes that have been:

• Exposed to warming temperatures exceeding 52C (125F); or

• Stored longer than 4 days within the warmer; or

• Been warmed, allowed to cool, and then re-warmed.

Other Information:

•When not in a warmer, store between 15-30˚C (59-86˚F)

Inactive Ingredients:

Allantoin, Aqua, 2-Bromo-2-Nitropropane-1, 3-Diol, Chlorphenesin, Decyl Glucoside, Glycerin, Polyaminopropyl Biguanide, Polysorbate 20, Propylene Glycol, Sodium Citrate